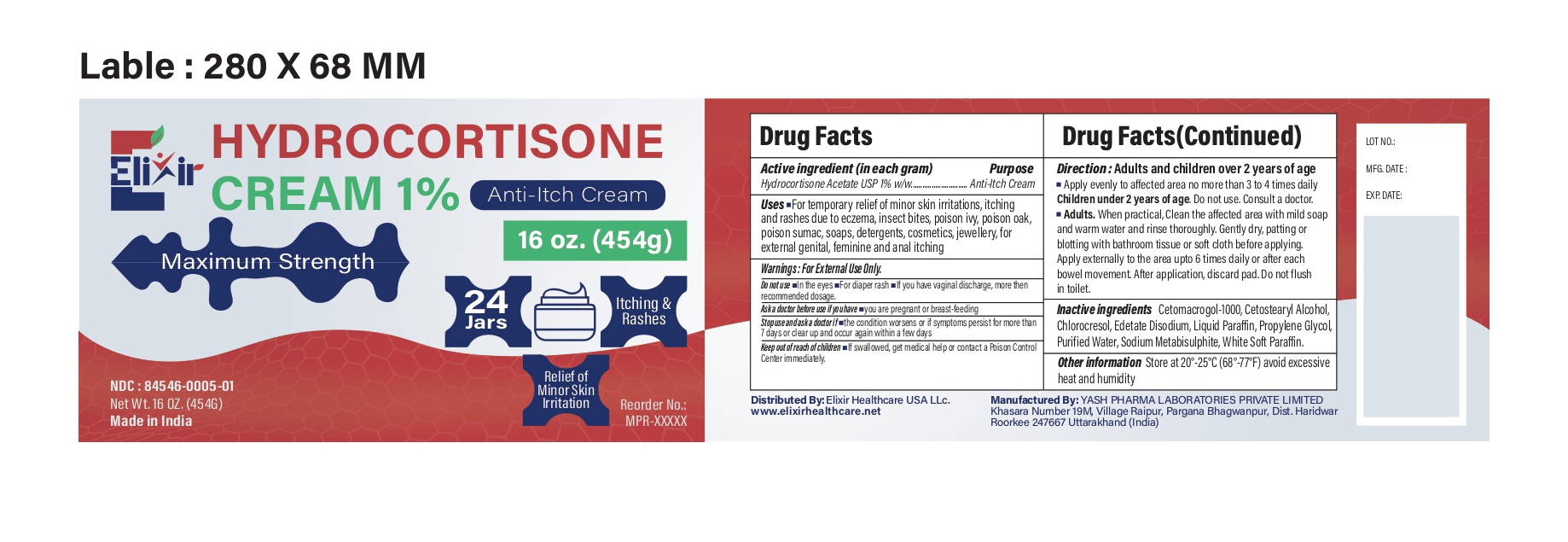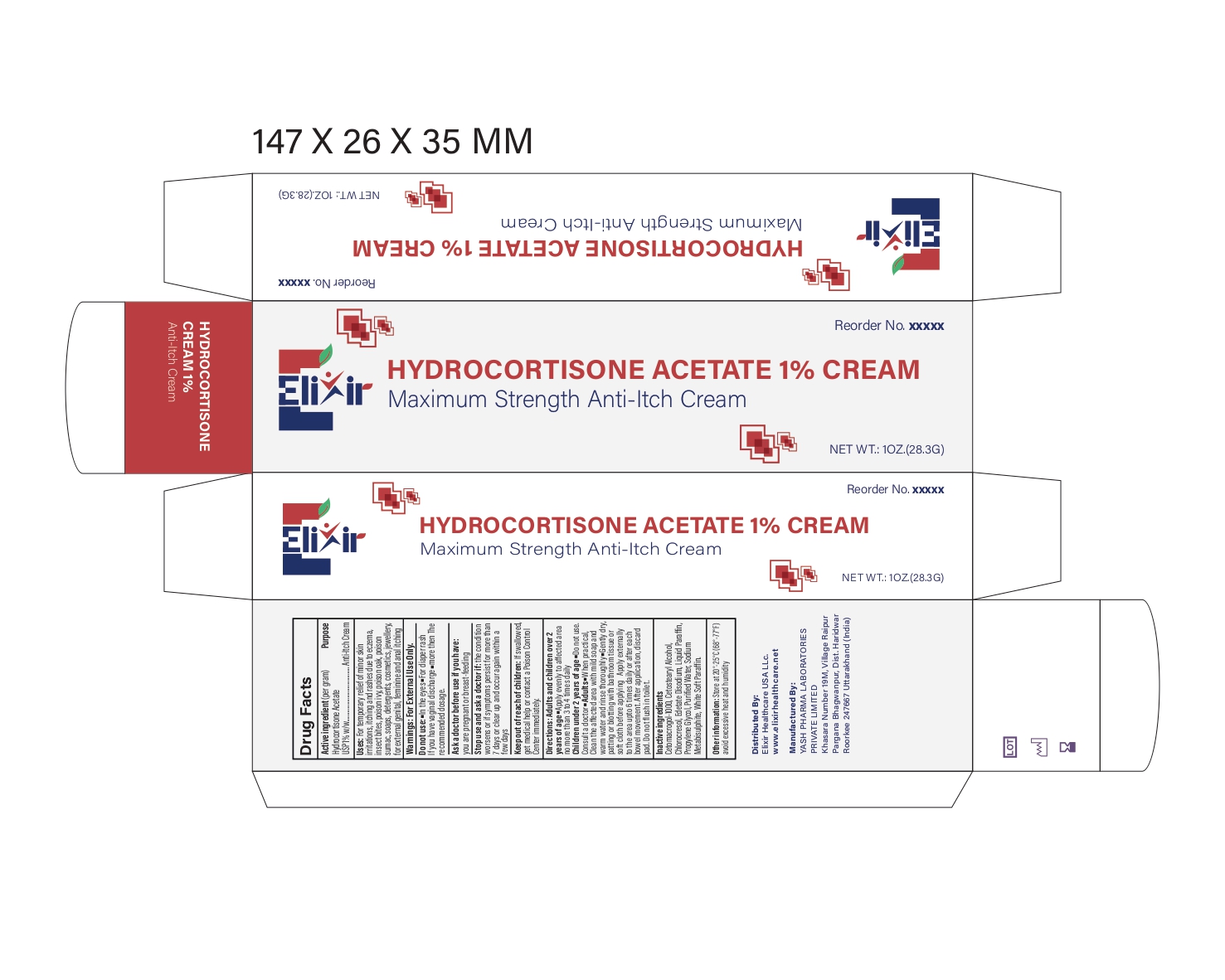 DRUG LABEL: ElixirCortiRelief
NDC: 84546-0005 | Form: CREAM
Manufacturer: ELIXIR HEALTHCARE USA, LLC.
Category: otc | Type: HUMAN OTC DRUG LABEL
Date: 20251202

ACTIVE INGREDIENTS: HYDROCORTISONE 1 g/100 g
INACTIVE INGREDIENTS: POLYETHYLENE GLYCOL 1000; CETOSTEARYL ALCOHOL; CHLOROCRESOL; EDETATE DISODIUM; MINERAL OIL; PROPYLENE GLYCOL; WATER; SODIUM METABISULFITE; PETROLATUM

Drug Facts Elixir CortiRelief

Active Ingredient (in each gram)

Hydrocortisone Acetate USP 1% w/w

Purpose

Anti-Itch Cream

Uses

For temporary relief of minor skin irritations, itching and rashes due to eczema, insect bites, poison ivy, poison oak, poison sumac, soaps, detergents, cosmetics, jewellery, for external genital, feminine and anal itching

Warnings

For external use only

Do not use

• In the eyes
• For diaper rash
If you have vaginal discharge, more then recommended dosage.

Ask a doctor before use in case of

• you are pregnant or breast-feeding

Stop use and ask a doctor if

• the condition worsens or if symptoms persist for more than 7 days or clear up and occur again within a few days

Keep out of reach of children

If swallowed, get medical help or contact a Poison Control Center right away.

Directions

Adults and children over 2 years of age
• Apply evenly to affected area no more than 3 to 4 times daily
Children under 2 years of age.Do not use. Consult a doctor.
• Adults.When practical, Clean the affected area with mild soap and warm water and rinse thoroughly. Gently dry, patting or blotting with bathroom tissue or soft cloth before applying. Apply externally to the area upto 6 times daily or after each bowel movement. After application, discard pad. Do not flush in toilet.

Inactive ingredients

Cetomacrogol-1000, Cetostearyl Alcohol, Chlorocresol, Edetate Disodium, Liquid Paraffin, Propylene Glycol, Purified Water, Sodium Metabisulphite, White Soft Paraffin.

Other information

Store at 20°-25°C (68°-77°F)
avoid excessive heat and humidity

PRINCIPAL DISPLAY PANEL

Reorder No. xxxx

Elixir

Hydrocortisone Cream 1%

Anti-Itch Cream

Net Wt. 1 OZ. (28.3G)

PRINCIPAL DISPLAY PANEL

Elixir

Hydrocortisone Cream 1%

Anti-Itch Cream

Maximum Strength

16 oz (454 g)

24 Jars

itching and rashes

Relief of minor skin irritation

NDC: 84546-0005-01

Net Wt. 16 OZ. 9454G)

Reorder No:

MPR-XXXXX